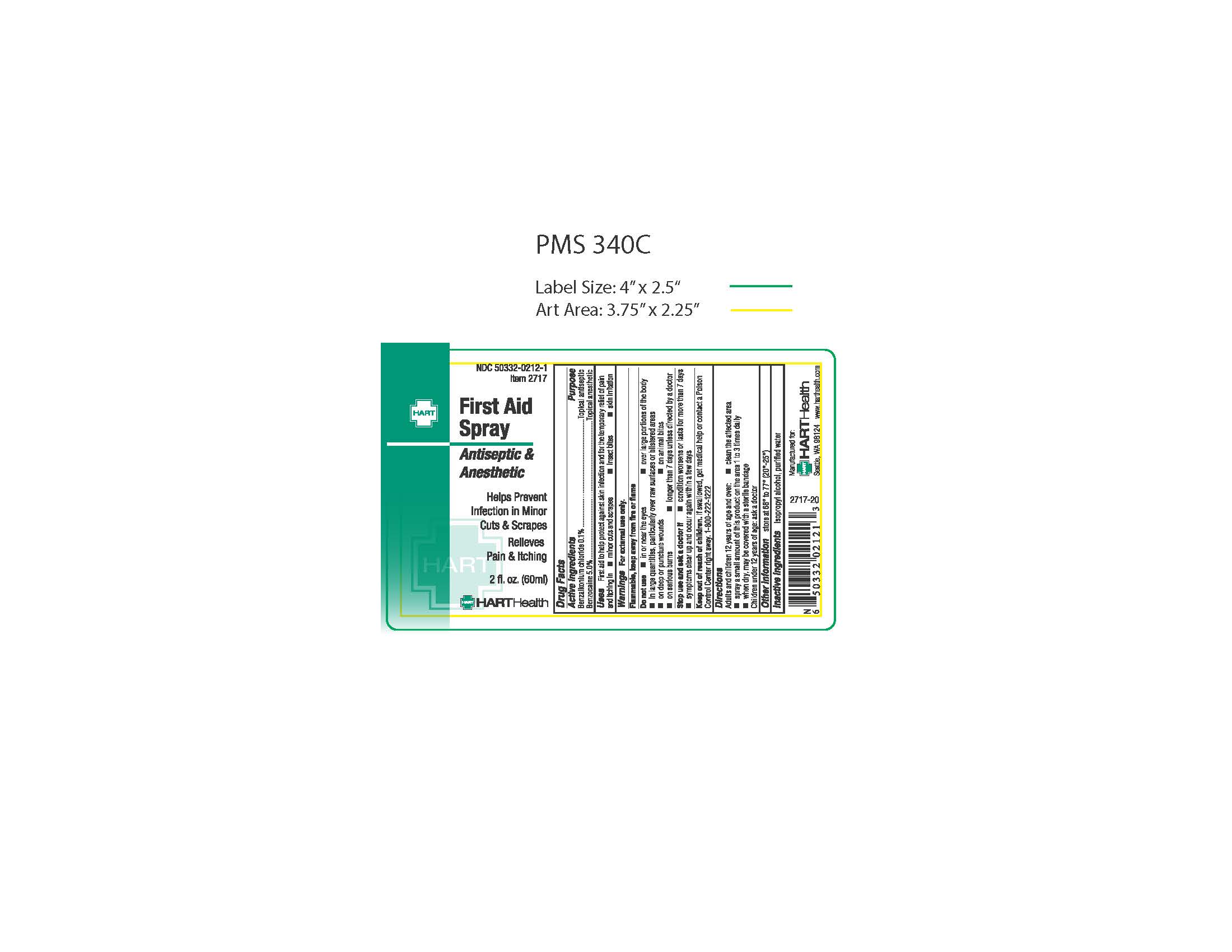 DRUG LABEL: First Aid
NDC: 50332-0212 | Form: SPRAY
Manufacturer: HART Health
Category: otc | Type: HUMAN OTC DRUG LABEL
Date: 20240118

ACTIVE INGREDIENTS: BENZALKONIUM CHLORIDE .001 mg/1 mg; BENZOCAINE .05 mg/1 mg
INACTIVE INGREDIENTS: ISOPROPYL ALCOHOL; WATER

FIRST AID SPRAY

Active Ingredients

Benzalkonium Chloride 0.1%

Benzocaine 5.0%

Purpose

Topical Antiseptic

Topical Anethetic

Uses

First aid to help protect against skin infection and for the temporary relief of pain and itching in

- minor cuts and scrapes
- bites
- skin irritation

Warnings

For external use only.

Flammable, keep away from heat or flame

Do not use

- in or near the eyes
- over large portions of the body
- in large quantities, particularly over raw surfaces or blistered areas
- on deep or puncture wounds
- on animal bites
- on serious burns
- longer than 7 days unless directed by a doctor

Stop use and ask a doctor if

- condition worsens
- symptoms persist for more than 7 days
- symptoms clear up and occur again within a few days

Keep out of reach of children. If swallowed, get medical help or contact a Poison Control Center right away. 1-800-222-1222

Directions

- clean affected area and spray 1 to 3 times daily
- may be covered with a sterile bandage

Children under 2 years of age: ask a doctor

Inactive Ingredients

Isopropyl Alcohol, Purified Water